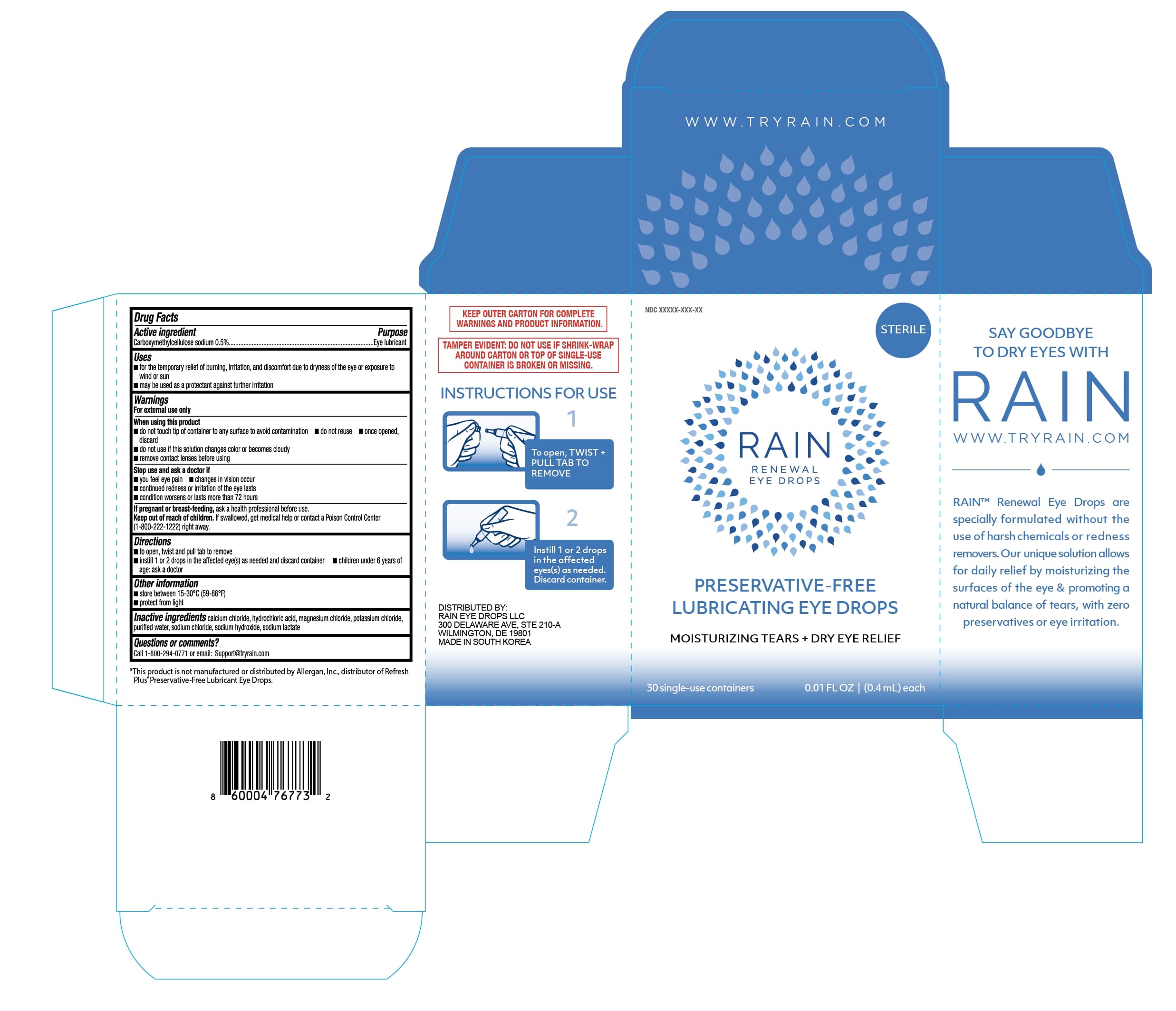 DRUG LABEL: Rain Renewal Eye Drops
NDC: 79662-002 | Form: SOLUTION/ DROPS
Manufacturer: Rain Eye Drops, LLC
Category: otc | Type: HUMAN OTC DRUG LABEL
Date: 20241002

ACTIVE INGREDIENTS: CARBOXYMETHYLCELLULOSE SODIUM, UNSPECIFIED FORM 0.5 g/100 mL
INACTIVE INGREDIENTS: SODIUM HYDROXIDE; CALCIUM CHLORIDE; MAGNESIUM CHLORIDE; SODIUM CHLORIDE; WATER; POTASSIUM CHLORIDE; SODIUM LACTATE; HYDROCHLORIC ACID

Rain Renewal Eye Drops - 30 ct

ACTIVE INGREDIENT

Carboxymethylcellulose sodium 0.5%

PURPOSE

Carboxymethylcellulose sodium.............Lubricant

INDICATIONS AND USAGE

- for the temporary relief of burning, irritation, and discomfort due to dryness of the eye or exposure to wind or sun
- may be used as a protectant against further irritation

Warnings

For external use only.

- to avoid contamination do not touch tip of container to any surface
- do not touch unit-dose tip to eye.
- do not reuse
- once opened, discard
- do not use if solution changes color or becomes cloudy.
- remove contact lenses before using

Stop Use and ASK Doctor if

- you feel eye pain
- changes in vision occurs
- continued redness or irritations of the eye last
- conditions worsens or last more than 72 hours

Stop use and ask a doctor if

- you experience eye pain
- changes in vision occur
- redness or irritation of the eye lasts
- conditions worsens or lasts more than 72 hours

Keep out of reach of children. If accidentally swallowed, get medical help or contact a Poison Control Center (1-800-222-1222) immediately.

Directions

- To open, twist and pull tab to remove
- Instill 1 or 2 drops in the affected eye(s) as needed and discard container
- Children under 6 years of age; ask a doctor

Other information

- Store at 15°-30°C (59°-86°F)
- Protect from light

RETAIN THIS CARTON FOR FUTURE REFERENCE

INACTIVE INGREDIENT

calcium chloride, hydrochloric acid, magnesium chloride, potassium chloride, purified water, sodium chloride, sodium hydroxide, sodium lactate.